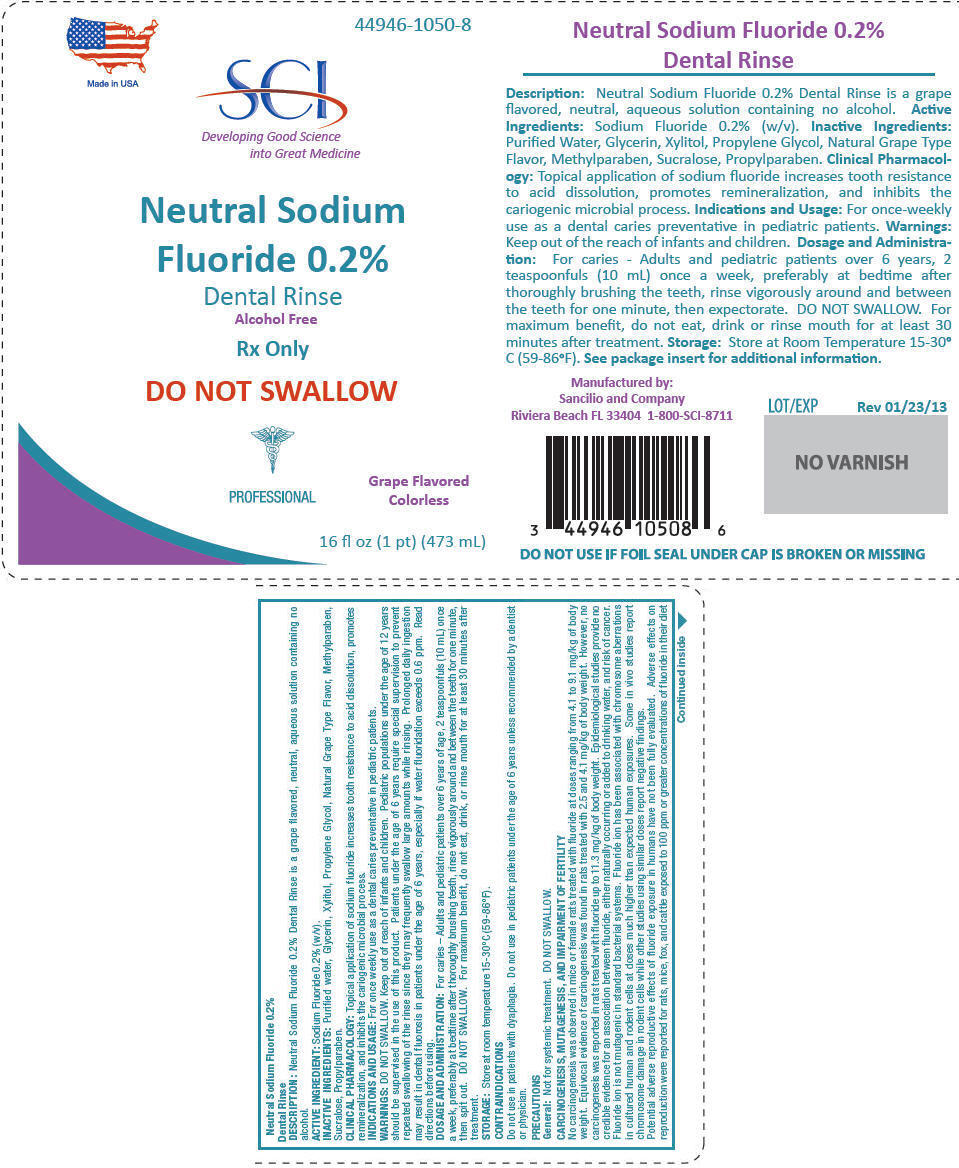 DRUG LABEL: Neutral Sodium Fluoride
NDC: 44946-1050 | Form: RINSE
Manufacturer: Sancilio & Company Inc
Category: prescription | Type: HUMAN PRESCRIPTION DRUG LABEL
Date: 20130128

ACTIVE INGREDIENTS: Sodium Fluoride 20 mg/1 mL
INACTIVE INGREDIENTS: Water; Glycerin; Xylitol; Propylene glycol; Methylparaben; Sucralose; Propylparaben

Neutral Sodium Fluoride 0.2%

Dental Rinse

DESCRIPTION

Neutral Sodium Fluoride 0.2% Dental Rinse is a grape flavored, neutral, aqueous solution containing no alcohol.

ACTIVE INGREDIENT: Sodium Fluoride 0.2% (w/v).

INACTIVE INGREDIENTS: Purified water, Glycerin, Xylitol, Propylene Glycol, Natural Grape Type Flavor, Methylparaben, Sucralose, Propylparaben.

CLINICAL PHARMACOLOGY

Topical application of sodium fluoride increases tooth resistance to acid dissolution, promotes remineralization, and inhibits the cariogenic microbial process.

INDICATIONS AND USAGE

For once weekly use as a dental caries preventative in pediatric patients.

WARNINGS

DO NOT SWALLOW. Keep out of reach of infants and children. Pediatric populations under the age of 12 years should be supervised in the use of this product. Patients under the age of 6 years require special supervision to prevent repeated swallowing of the rinse since they may frequently swallow large amounts while rinsing. Prolonged daily ingestion may result in dental fluorosis in patients under the age of 6 years, especially if water fluoridation exceeds 0.6 ppm. Read directions before using.

DOSAGE AND ADMINISTRATION

For caries – Adults and pediatric patients over 6 years of age, 2 teaspoonfuls (10 mL) once a week, preferably at bedtime after thoroughly brushing teeth, rinse vigorously around and between the teeth for one minute, then spit out. DO NOT SWALLOW. For maximum benefit, do not eat, drink, or rinse mouth for at least 30 minutes after treatment.

STORAGE

Store at room temperature 15-30°C (59-86°F).

CONTRAINDICATIONS

Do not use in patients with dyaphagia. Do not use in pediatric patients under the age of 6 years unless recommended by a dentist or physician.

PRECAUTIONS

General

Not for systemic treatment. DO NOT SWALLOW.

CARCINOGENESIS, MUTAGENESIS, AND IMPAIRMENT OF FERTILITY

No carcinogenesis was observed in mice or female rats treated with fluoride at doses ranging from 4.1 to 9.1 mg/kg of body weight. Equivocal evidence of carcinogenesis was found in rats treated with 2.5 and 4.1 mg/kg of body weight. However, no carcinogenesis was reported in rats treated with fluoride up to 11.3 mg/kg of body weight. Epidemiological studies provide no credible evidence for an association between fluoride, either naturally occurring or added to drinking water, and risk of cancer. Fluoride ion is not mutagenic in standard bacterial systems. Fluoride ion has been associated with chromosome aberrations in cultured human and rodent cells at doses much higher than expected human exposures. Some in vivo studies report chromosome damage in rodent cells while other studies using similar doses report negative findings.

Potential adverse reproductive effects of fluoride exposure in humans have not been fully evaluated. Adverse effects on reproduction were reported for rats, mice, fox, and cattle exposed to 100 ppm or greater concentrations of fluoride in their diet or drinking water. Studies conducted in rats have shown that lower concentrations of fluoride (5 mg/kg of body weight) did not result in impaired fertility or reproductive capabilities.

PREGNANCY

Teratogenic Effects

Pregnancy Category B

Fluoride crosses the placenta in rats, but only 0.01% of the amount administered is incorporated in fetal tissue. Animal studies with rats, mice, and rabbits have demonstrated that fluoride is not teratogenic. Maternal exposure to 12.2 mg fluoride/kg of body weight in rats or 13.1 mg/kg of body weight in rabbits did not affect litter size or fetal weight and did not increase the frequency of skeletal or visceral malformations. No adequate or well-controlled studies have been conducted in pregnant women. Epidemiological studies conducted in areas with high levels of naturally occurring fluoridated water have shown no increase in birth defects. Heavy exposure during in utero development may result in skeletal fluorosis which becomes evident in childhood.

NURSING MOTHERS

It is not known whether fluoride is excreted in human milk. However, many drugs are excreted in human milk and caution should be exercised when fluoride products are administered to nursing women. Reduced milk production was reported in farm-raised fox when they were fed a diet containing a high concentration of fluoride (98-137 mg/kg of body weight). No adverse effects on parturition, lactation, or offspring were observed in rats administered fluoride up to 5 mg/kg of body weight.

PEDIATRIC USE

The use of Neutral Sodium Fluoride 0.2% Dental Rinse as a weekly caries preventative product in pediatric patients aged 6 to 16 years is supported by adequate and well-controlled clinical trials in students aged 6 to 12 years.1-3 Safety and efficacy in pediatric patients below the age of 6 years have not been established (refer to CONTRAINDICATIONS AND WARNINGS sections).

GERIATRIC USE

Of the total number of subjects considered in clinical trials using 1.1% (w/v) sodium fluoride, 15% were 65 years and older, while 1% were 75 years and older. Overall, no differences in safety or efficacy were observed between these subjects and younger subjects. Other reported clinical data have not identified differences in responses between the elderly and younger patients but greater sensitivity in some older individuals cannot be ruled out. Fluoride is known to be substantially excreted by the kidney, and the risk of toxic reactions may be greater in patients with impaired renal function. Since elderly patients are more likely to have decreased renal function, care should be taken in dose selection. It may be useful to monitor renal function.

ADVERSE REACTIONS

In patients with mucositis, gingival tissues may be hypersensitive to flavor present in the formulation. Allergic reactions are rarely reported.

OVERDOSE

Accidental ingestion of large amounts of fluoride may result in acute burning in the mouth and sore tongue. Nausea, vomiting, and diarrhea may occur soon after ingestion (within 30 minutes) and are accompanied by salivation, hematemesis and epigastric cramping abdominal pain. These symptoms may persist for 24 hours. If less than 5 mg fluoride/kg body weight (i.e., less than 2.3 mg fluoride/pound body weight) has been ingested, give calcium in the form of milk orally to relieve gastrointestinal symptoms and observe for a few hours. If more than 5 mg fluoride body weight (i.e., more than 2.3 mg fluoride/pound body weight) has been ingested, induce vomiting, administer orally soluble calcium in the form of milk, calcium gluconate or calcium lactate solution, and immediately seek medical assistance. For accidental ingestion of more than 15 mg fluoride/kg body weight (i.e., more than 6.9 mg fluoride/pound body weight) induce vomiting, and admit immediately to a hospital facility.

A treatment dose (10 mL) or two teaspoonfuls) of Neutral Sodium Fluoride 0.2% Dental Rinse contains approximately 9 mg of fluoride. One 16 fl oz bottle contains approximately 429 mg fluoride.

DOSAGE AND ADMINISTRATION

For caries – Adults and pediatric patients over 6 years of age, 2 teaspoonfuls (10 mL) once a week, preferably at bedtime after thoroughly brushing teeth, rinse vigorously around and between the teeth for one minute, then spit out. DO NOT SWALLOW. For maximum benefit, do not eat, drink, or rinse mouth for at least 30 minutes after treatment.

HOW SUPPLIED

Plastic bottle with child-resistant closure containing 16 fl oz (473 mL).

STORAGE

Store at room temperature 15-30°C (59-86°F).

REFERENCES

1. American Dental Association, Accepted Dental Therapeutics, Ed. 4, Chicago (1984):403.
2. Ibid., pp. 405-407.
3. L.W. Ripa, G.S. Leske, and A. Sposato, "Supervised Weekly Rinsing with a 0.2% Neutral NaF Solution: Final Results of a Demonstration Program after Six School Years," J. Pub. Health Dent. 1984;43:53-62.
4. W.S. Driscoll, et al., "Caries-Preventative Effects on School Children Daily and Weekly Fluoridate Mouthrinsing in a Fluoridated Community: Final Results after 30 Months," JADA 1982;105:1010-013.

Manufactured by:
Sancilio and Company
Riviera Beach, FL 33404

PRINCIPAL DISPLAY PANEL - 473 mL Bottle Label

Made in USA

44946-1050-8

SCI

Developing Good Science
into Great Medicine

Neutral Sodium

Fluoride 0.2%

Dental Rinse
Alcohol Free

Rx Only

DO NOT SWALLOW

PROFESSIONAL

Grape Flavored
Colorless

16 fl oz (1 pt) (473 mL)